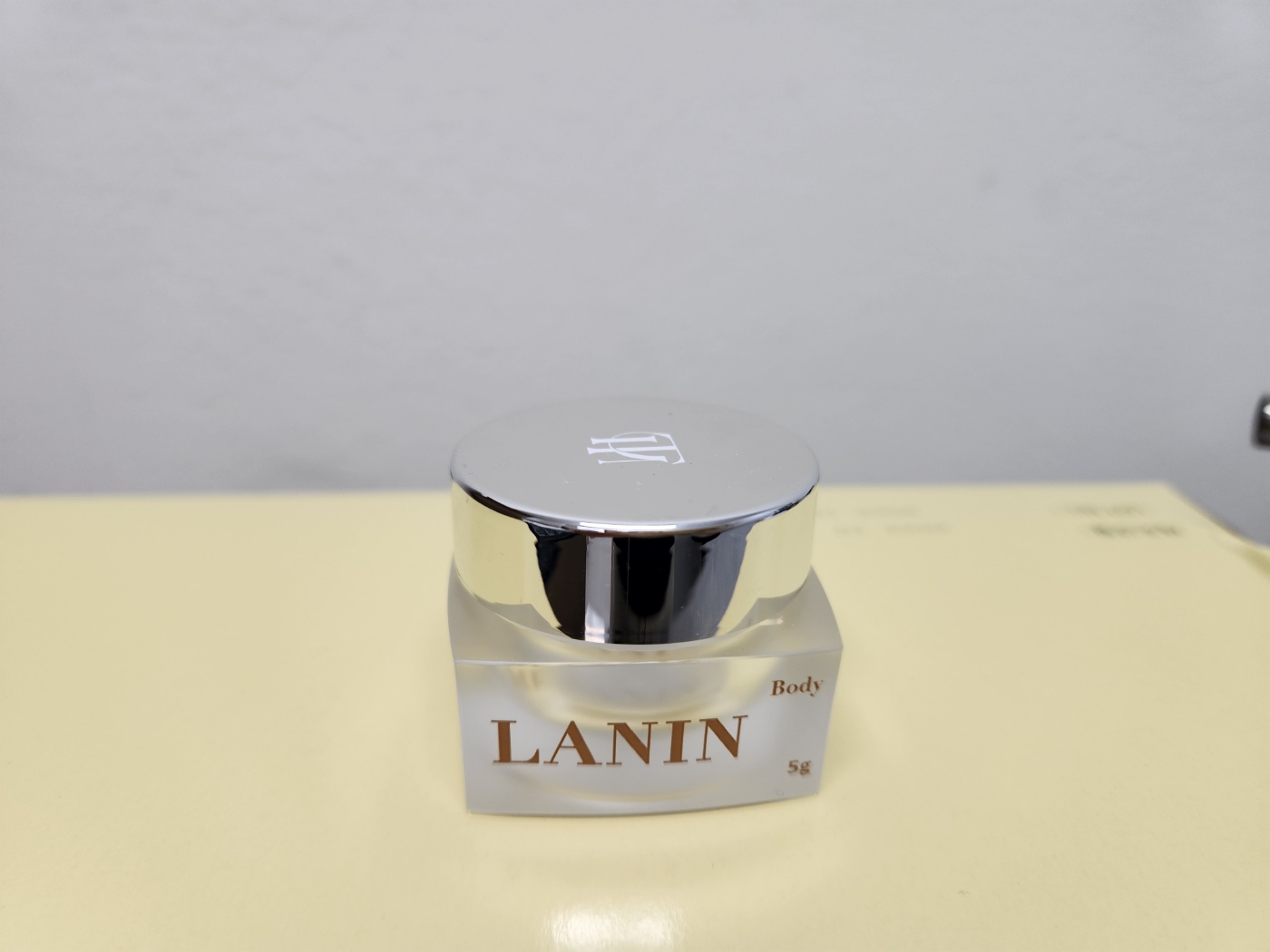 DRUG LABEL: The Melanin Skin Protectant Cream
NDC: 85514-6539 | Form: CREAM
Manufacturer: Reedfresh Co., LTD
Category: otc | Type: HUMAN OTC DRUG LABEL
Date: 20250501

ACTIVE INGREDIENTS: ALLANTOIN 1 g/100 g
INACTIVE INGREDIENTS: WATER 1 g/100 g

The Melanin Skin Protectant Cream

Active Ingredients

Allantoin

Inactive ingredients:

Purified Water, Glycerin, Propylene Glycol, Laurocapram, Niacinamide, Xanthan Gum, Butylene Glycol, Tocopherol, Cetearyl Alcohol, Isohexadecane, Ethylhexyl Palmitate, Caprylic/Capric Triglyceride, Hydrogenated Lecithin, Cetearyl Glucoside, Polyacrylamide, C13-14 Isoparaffin, 1,2-Hexanediol, Disodium EDTA, Ergothioneine, Selaginella Tamariscina Extract, Ethylhexylglycerin, Glucose, Fragrance, Ginkgo Biloba Leaf Extract, Prunella Vulgairs Extract, Croton Lechleri Resin Extract

PURPOSE

Temporarily protects and helps relieve minor skin irritations
Helps protect chapped or cracked skin

WARNINGS

For external use only
Do not use on deep or puncture wounds, animal bites, or serious burns unless directed by a doctor
Discontinue use and consult a dermatologist if any of the following symptoms occur, as continued use may worsen the condition: 1) Red spots, swelling, itching, or irritation during use; 2) Similar symptoms appearing on the applied area due to direct sunlight exposure
Avoid contact with eyes; if contact occurs, rinse immediately
Keep out of reach of children
Store in a cool, dry place, away from direct sunlight and extreme temperatures

These highlights do not include all the information needed to use. See full prescribing information.

Apply as needed

KEEP OUT OF THE REACH OF CHILDREN.

RECENT MAJOR CHANGES

Newly added

INDICATIONS AND USAGE

Temporarily protects and helps relieve minor skin irritations
Helps protect chapped or cracked skin